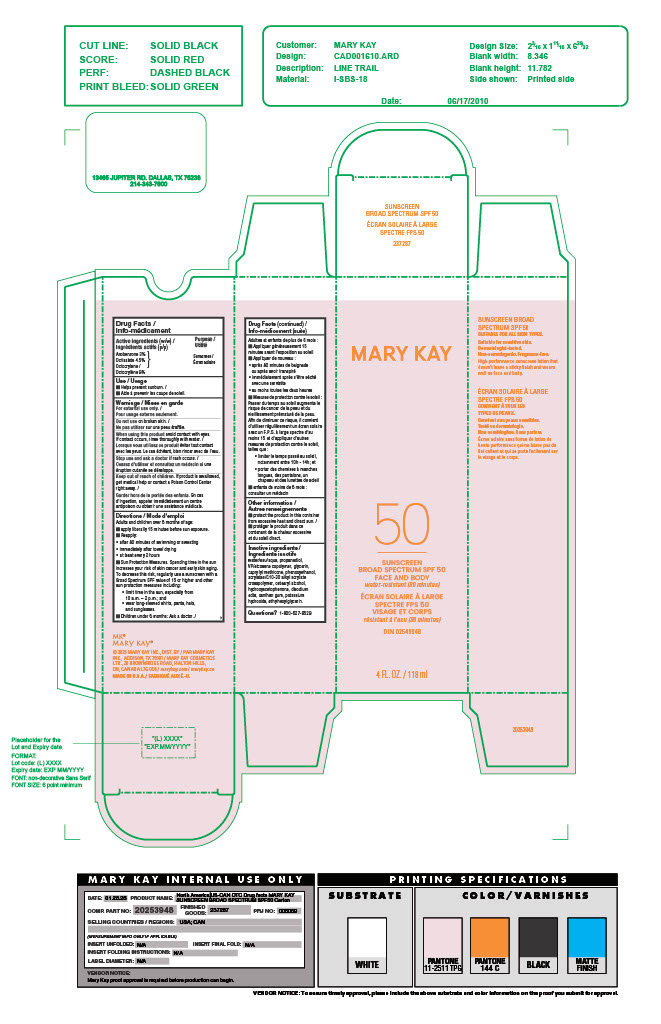 DRUG LABEL: SUNSCREEN BROAD SPECTRUM SPF 50 FACE AND BODY
NDC: 51531-7287 | Form: LOTION
Manufacturer: Mary Kay Inc.
Category: otc | Type: HUMAN OTC DRUG LABEL
Date: 20250122

ACTIVE INGREDIENTS: OCTOCRYLENE 9 g/100 g; AVOBENZONE 3 g/100 g; OCTISALATE 4.5 g/100 g
INACTIVE INGREDIENTS: CAPRYLYL METHICONE; ACRYLATES/C10-30 ALKYL ACRYLATE CROSSPOLYMER (60000 MPA.S); ETHYLHEXYLGLYCERIN; GLYCERIN; CETEARYL ALCOHOL; POTASSIUM HYDROXIDE; VINYLPYRROLIDONE/EICOSENE COPOLYMER; WATER; PROPANEDIOL; EDETATE DISODIUM; XANTHAN GUM; PHENOXYETHANOL; HYDROXYACETOPHENONE

Active Ingredients

Avobenzone 3% (w/w)

Octisalate 4.5% (w/w)

Octocrylene 9% (w/w)

Purpose

Sunscreen

Uses

Helps prevent sunburn.

Warnings

Do not use

on broken skin.

When using this product

avoid contact with eyes. If contact occurs, rinse thoroughly with water.

Stop use and ask a doctor

if rash occurs.

Keep out of reach of children.

If product is swallowed, get medical help or contact a Poison Control Center right away.

Directions

Adults and children over 6 months of age: ■ apply liberally 15 minutes before sun exposure. ■ Reapply: • after 80 minutes of swimming or sweating • immediately after towel drying • at least every 2 hours ■ Sun Protection Measures. Spending time in the sun increases your risk of skin cancer and early skin aging. To decrease this risk, regularly use a sunscreen with a Broad Spectrum SPF value of 15 or higher and other sun protection measures including: • limit time in the sun, especially from 10 a.m. – 2 p.m.; and • wear long-sleeved shirts, pants, hats, and sunglasses. ■ Children under 6 months: Ask a doctor.

Other information

■ protect the product in this container from excessive heat and direct sun.

Inactive ingredients

water/eau/aqua, propanediol, VP/eicosene copolymer, glycerin, caprylyl methicone, phenoxyethanol, acrylates/C10-30 alkyl acrylate crosspolymer, cetearyl alcohol, hydroxyacetophenone, disodium edta, xanthan gum, potassium hydroxide, ethylhexylglycerin.

Questions?

1-800-627-9529

PACKAGE LABEL

MARY KAY

50

SUNSCREEN BROAD SPECTRUM SPF 50 FACE AND BODY water-resistant (80 minutes)

4 FL. OZ. / 118 mL